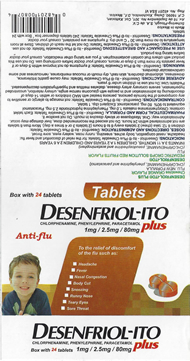 DRUG LABEL: Desenfriol-D
NDC: 53666-517 | Form: TABLET
Manufacturer: Salimex, S.A.
Category: otc | Type: HUMAN OTC DRUG LABEL
Date: 20210623

ACTIVE INGREDIENTS: CHLORPHENIRAMINE MALEATE 0.001 g/1 g; PHENYLEPHRINE HYDROCHLORIDE 0.0025 g/1 g; ACETAMINOPHEN 0.08 g/1 g
INACTIVE INGREDIENTS: FD&C BLUE NO. 1; FD&C RED NO. 40; WATER; SORBITOL; ANHYDROUS CITRIC ACID; CARBOXYMETHYLCELLULOSE SODIUM; SODIUM BENZOATE; SUCROSE; GLYCERIN; MICROCRYSTALLINE CELLULOSE; XANTHAN GUM; D&C RED NO. 33

Desenfriol-Ito

Active ingredient (in each caplet)

CHLORPHENIRAMINE MALEATE 2.0 mg

PHENYLEPHRINE HYDROCHLORIDE 5.0 mg

ACETAMINOPHEN 500 mg

Purpose

Pain reliever

Antihistamine

Nasal decongestant

Uses

- temporarily relieves these symptoms of hay fever or other upper respiratory allergies:
- headache
- sinus congestion and pressure
- nasal congestion
- runny nose and sneezing
- minor aches and pains
- temporarily relieves these additional symptoms of hay fever:
- itching of the nose or throat
- itchy, watery eyes
- helps clear nasal passages
- helps decongest sinus openings and passages

Warnings

- Liver warning: This product contains acetaminophen. Severe liver damage may occur if you take
- more than 4,000 mg of acetaminophen in 24 hours
- with other drugs containing acetaminophen
- 3 or more alcoholic drinks every day while using this product
- Allergy alert: Acetaminophen may cause severe skin reactions. Symptoms may include:
- skin reddening
- blisters
- rash
- If a skin reaction occurs, stop use and seek medical help right away.

Do not use

- with any other drug containing acetaminophen (prescription or nonprescription). If you are not sure whether a drug contains acetaminophen, ask a doctor or pharmacist.
- if you are now taking a prescription monoamine oxidase inhibitor (MAOI) (certain drugs for depression, psychiatric, or emotional conditions, or Parkinson’s disease), or for 2 weeks after stopping the MAOI drug. If you do not know if your prescription drug contains an MAOI, ask a doctor or pharmacist before taking this product.
- if you have ever had an allergic reaction to this product or any of its ingredients
- to make a child sleepy

Ask a doctor before use if you have

- liver disease
- heart disease
- high blood pressure
- thyroid disease
- diabetes
- trouble urinating due to an enlarged prostate gland
- a breathing problem such as emphysema or chronic bronchitis
- glaucoma

Ask a doctor or pharmacist before use if you are

- taking the blood thinning drug warfarin
- taking sedatives or tranquilizers

When using this product

- do not exceed recommended dosage
- excitability may occur, especially in children
- drowsiness may occur
- alcohol, sedatives, and tranquilizers may increase drowsiness
- avoid alcoholic drinks
- be careful when driving a motor vehicle or operating machinery

Stop use and ask a doctor if

- nervousness, dizziness, or sleeplessness occur
- pain or nasal congestion gets worse or lasts more than 7 days
- fever gets worse or lasts more than 3 days
- redness or swelling is present
- new symptoms occur

These could be signs of a serious condition.otc

If pregnant or breast-feeding,

ask a health professional before use.

Keep out of reach of children.

Overdose warning: In case of overdose, get medical help or contact a Poison Control Center right away (1-800-222-1222). Quick medical attention is critical for adults as well as for children even if you do not notice any signs or symptoms.

Directions

do not take more than directed (see overdose warning)

adults and children 12 years and over

- take 2 caplets every 4-6 hours
- swallow whole – do not crush, chew or dissolve
- do not take more than 10 caplets in 24 hours

children under 12 years

- ask a doctor

Inactive ingredients

anhydrous citric acid, carboxymethylcellulose sodium, D&C red #33, FD&C blue #1, FD&C red 40, flavors, glycerin, microrocrystalline cellulose, purified water, sodium benzoate, sorbitol, sucrose, xanthan gum